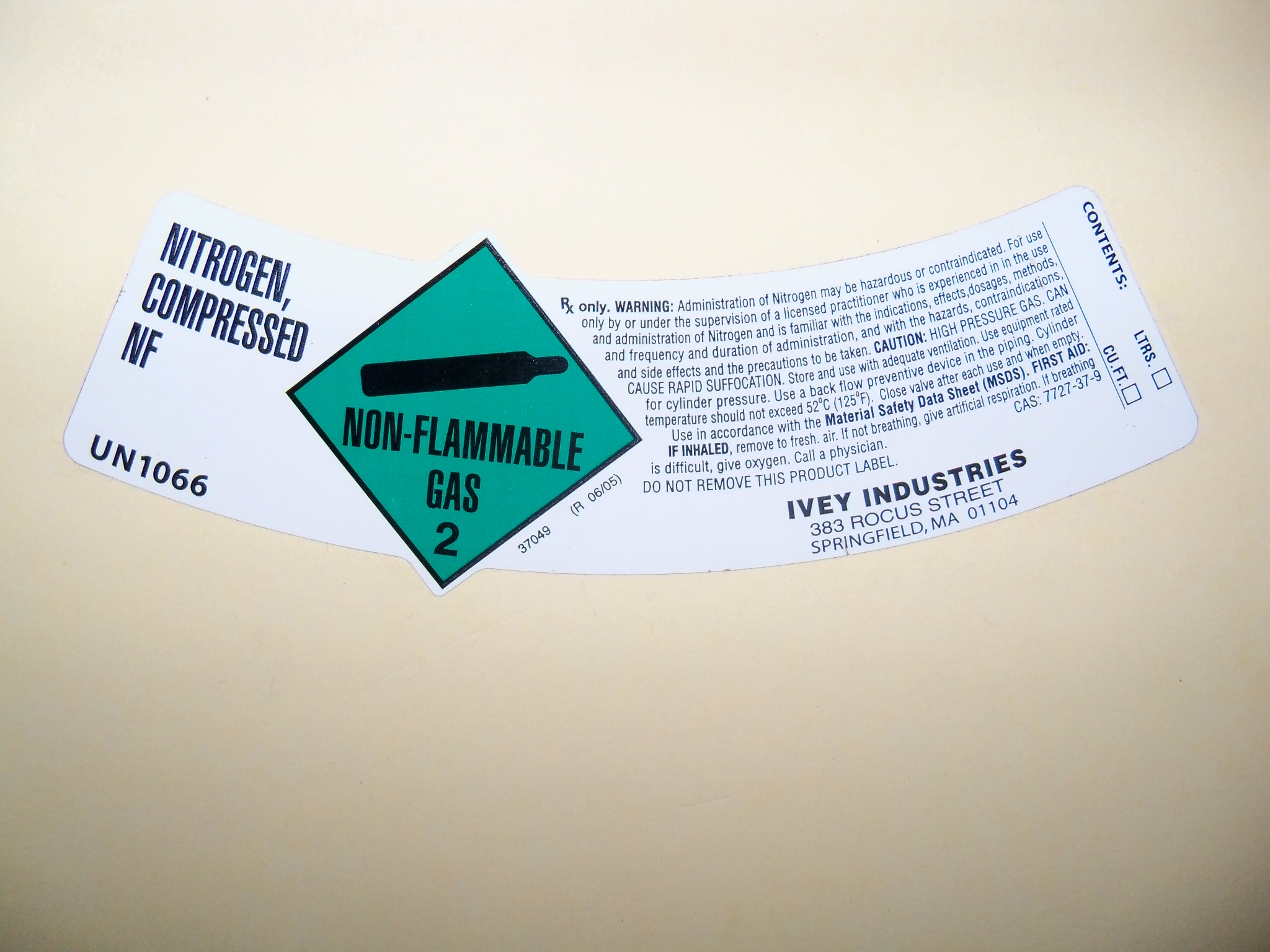 DRUG LABEL: nitrogen
NDC: 55065-003 | Form: GAS
Manufacturer: Ivey Industries
Category: prescription | Type: HUMAN PRESCRIPTION DRUG LABEL
Date: 20100503

ACTIVE INGREDIENTS: nitrogen 99 L/100 L

NITROGEN COMPRESSED NF

PACKAGE LABEL

NITROGEN COMPRESSED NF
UN 1066